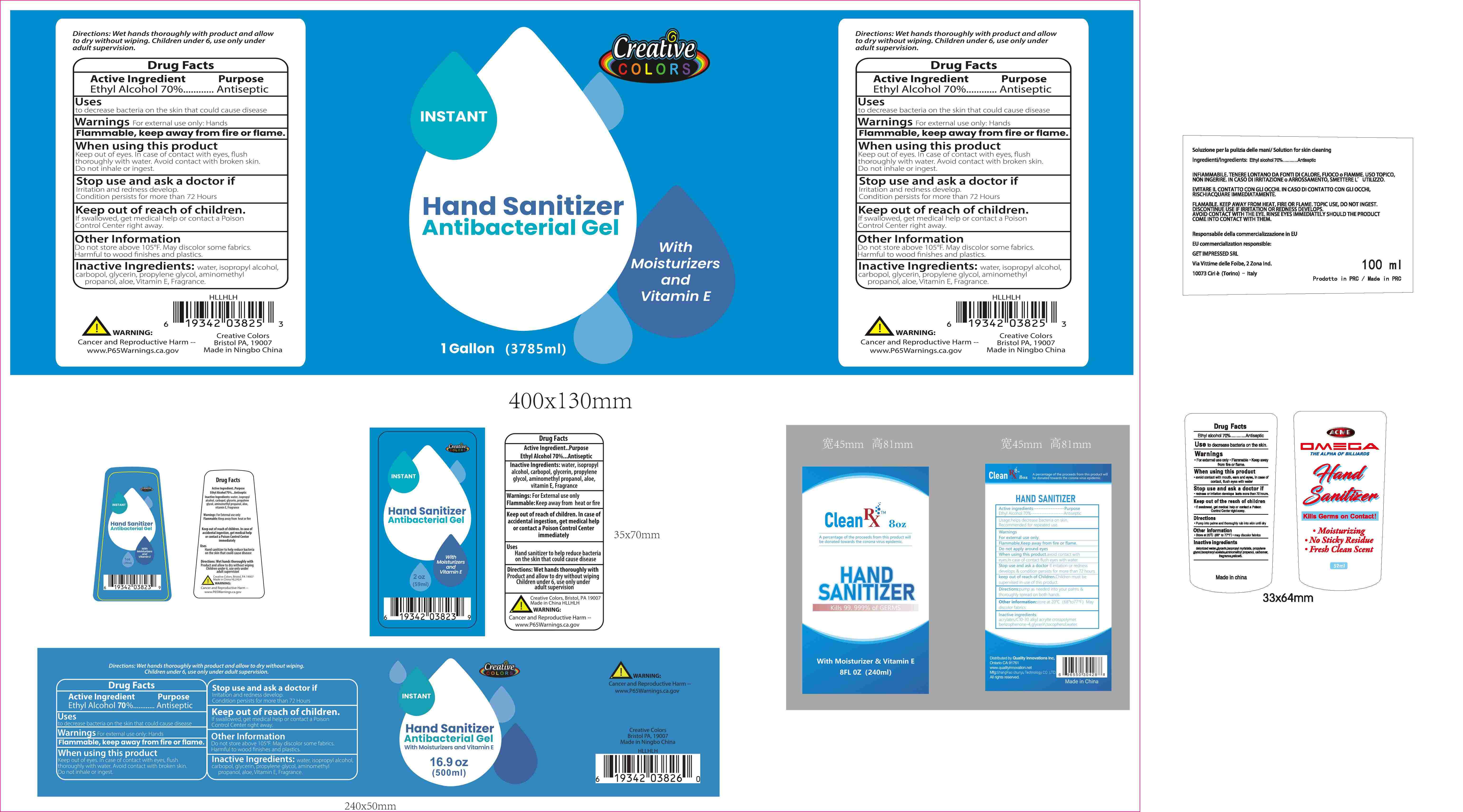 DRUG LABEL: Hand Sanitizer Antibacterial Gel
NDC: 72922-012 | Form: GEL
Manufacturer: ShangRao chunyu Technology CO.,LTD.
Category: otc | Type: HUMAN OTC DRUG LABEL
Date: 20200407

ACTIVE INGREDIENTS: ALCOHOL 70 mL/100 mL
INACTIVE INGREDIENTS: ALPHA-TOCOPHEROL; GLYCERIN; WATER; CARBOMER HOMOPOLYMER TYPE C (ALLYL PENTAERYTHRITOL CROSSLINKED); ISOPROPYL ALCOHOL; PROPYLENE GLYCOL; ALOE; AMINOMETHYLPROPANOL

Active Ingredien

Ethyl Alcohol 70% Antiseptic

Keep out of reach of children

If swallowed, contact a physician or poison control center.

purpose

Antiseptic

Warnings

External use only, Not to take orally.
seek professional help if skin gets allergic to the alcohol

DISPOSAL AND WASTE HANDLING

Do not sote above 110 oF

INDICATIONS&USAGE

Apply a few drops of gel on the hand and rub them thoroughly.

DOSAGE&ADMINISTRATION

29ML